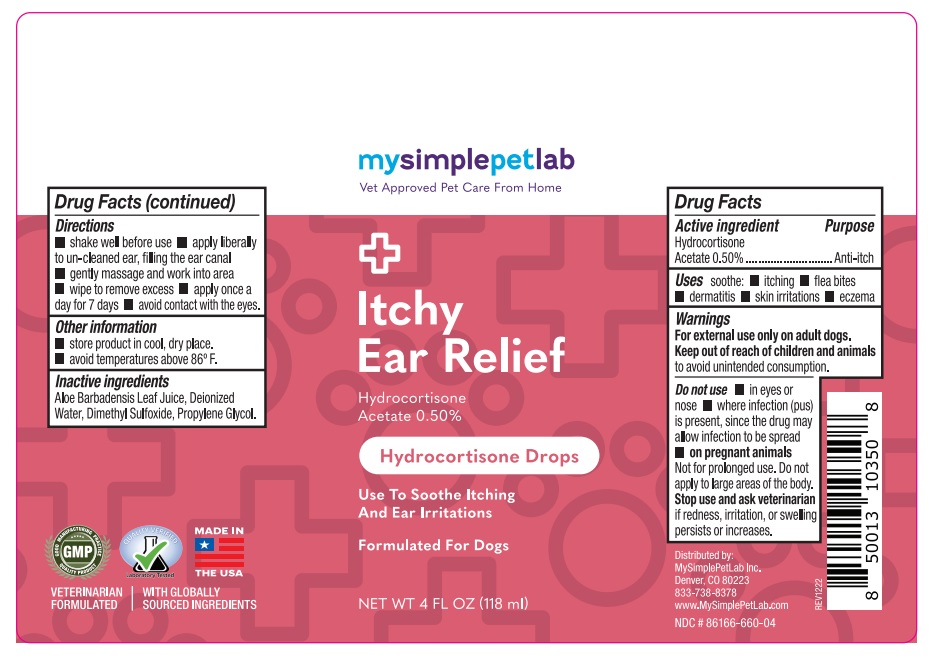 DRUG LABEL: MySimplePetLab Itchy Ear Relief
NDC: 86166-660 | Form: SOLUTION/ DROPS
Manufacturer: Mysimplepetlab Inc
Category: animal | Type: OTC ANIMAL DRUG LABEL
Date: 20230316

ACTIVE INGREDIENTS: HYDROCORTISONE ACETATE 0.5 g/100 mL
INACTIVE INGREDIENTS: ALOE VERA LEAF; WATER; DIMETHYL SULFOXIDE; PROPYLENE GLYCOL

mysimplepetlab Itchy Ear Relief

Active ingredient

Hydrocortisone Acetate 0.50%

Purpose

Anti-itch

Uses

soothe: • itching • flea bites • dermatitis • skin irritations • eczema

Warnings

For external use on adult dogs.
Keep out of reach of children and animals to avoid unintended consumption.

Do not use • in eyes or nose • where infection (pus) is present, since the drug may allow infection to be spread
• on pregnant animals
Not for prolonged use. Do not apply to large areas of the body.
Stop use and ask veterinarian if redness, irritation, or swelling persists or increases.

Directions

• shake well before use • apply liberally to un-cleaned ear, filling the ear canal • gently massage and work into area • wipe to remove excess. • apply once a day for 7 days • avoid contact with the eyes.

Other information

- store product in a cool, dry place.
- avoid temperatures above 86° F.

Inactive ingredients

Aloe Barbadensis Leaf Juice, Deionized Water, Dimethyl Sulfoxide, Propylene Glycol.

Vet Approved Pet Care From Home

Use to Soothe Itching and Ear Irritations

Formulated for Dogs

Distributed by:
MySimplePetLab Inc.
Denver, CO 80223
833-738-8378
www.MySimplePetLab.com

VETERINARIANS FORMULATED

WITH GLOBALLY SOURCED INGREDIENTS

MADE IN THE USA